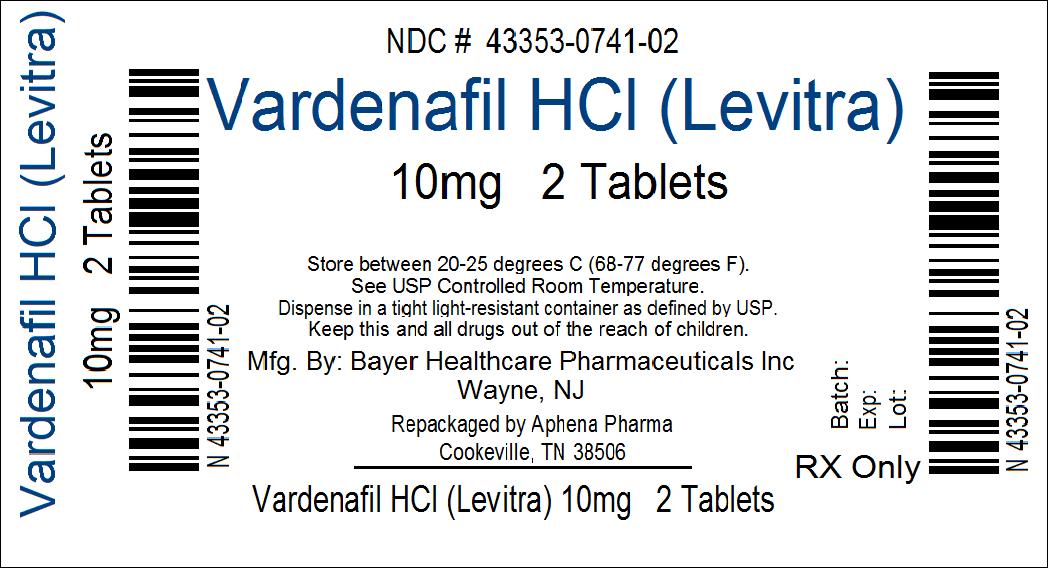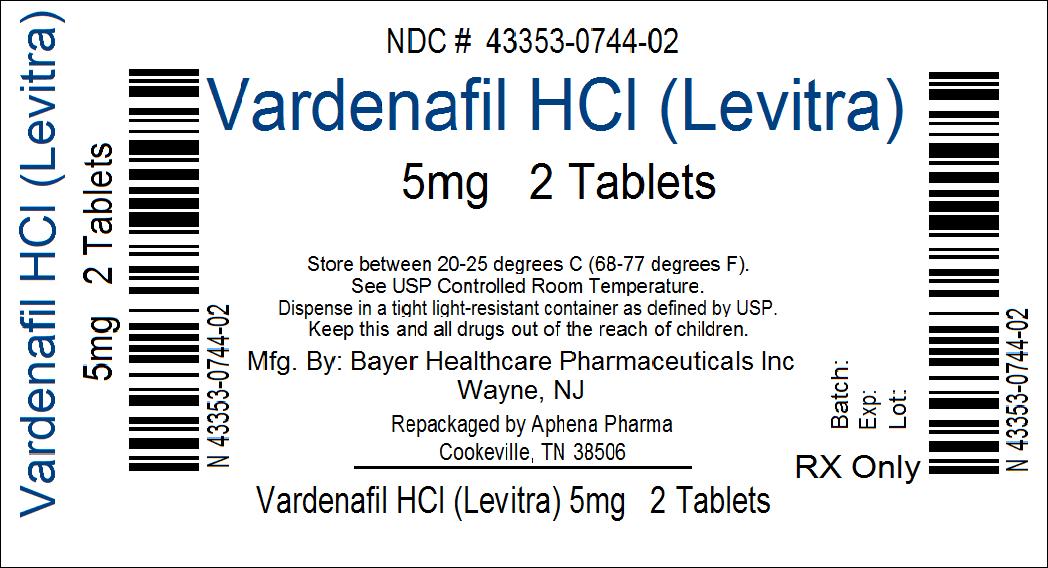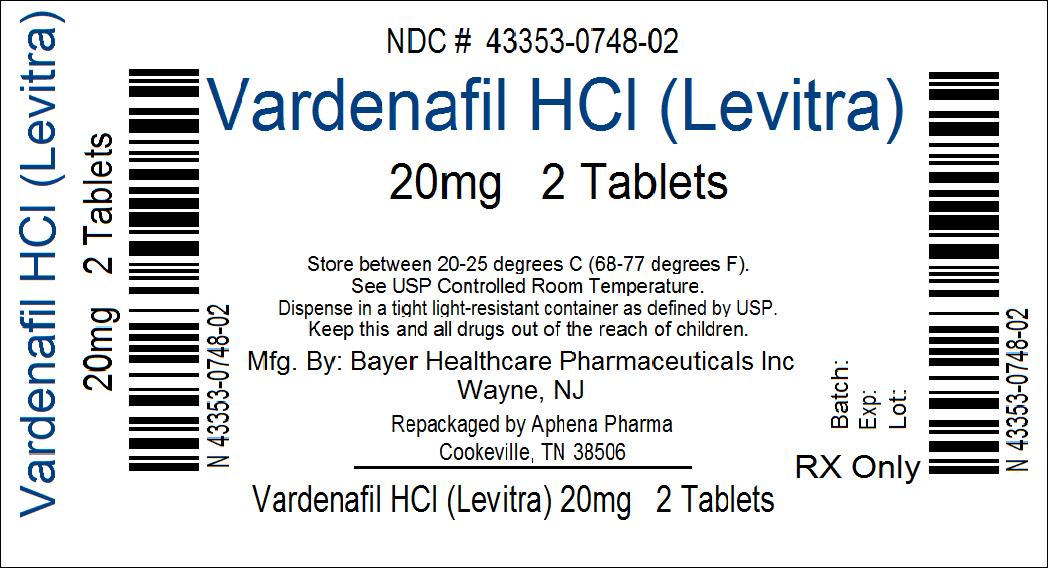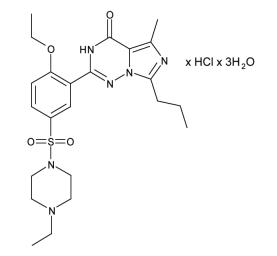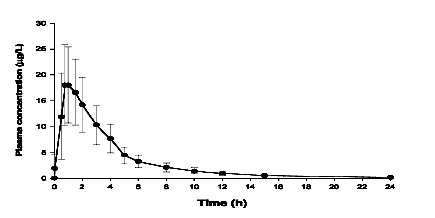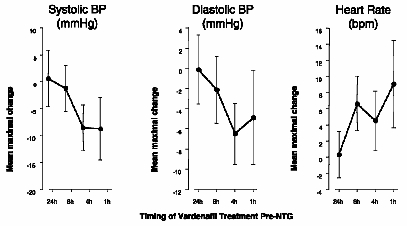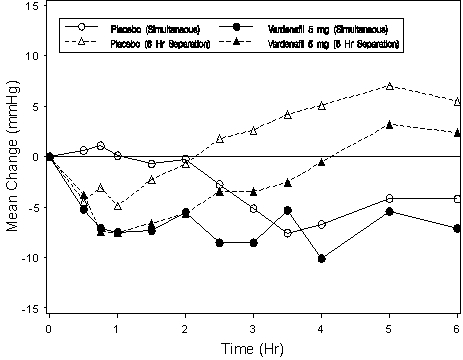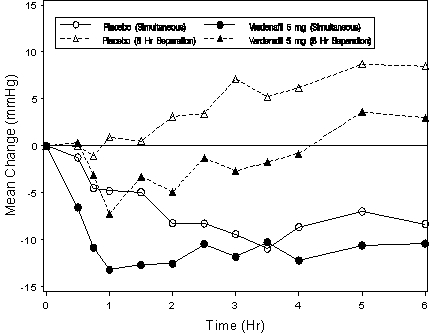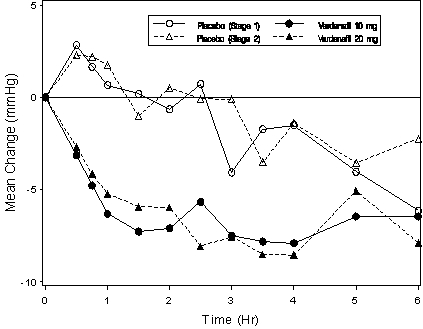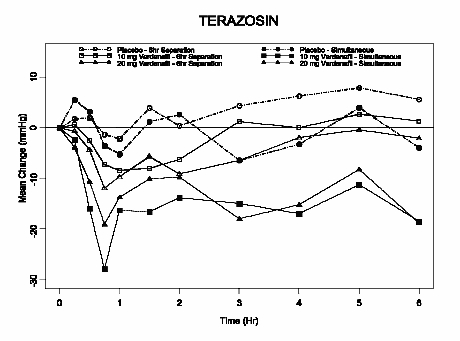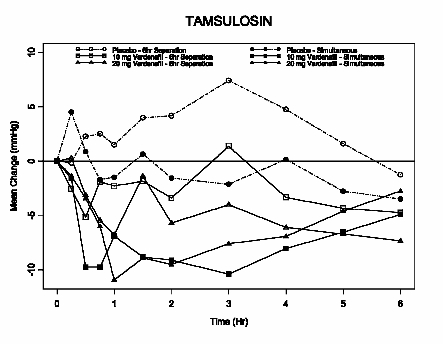 DRUG LABEL: Levitra
NDC: 43353-744 | Form: TABLET, FILM COATED
Manufacturer: APHENA PHARMA SOLUTIONS - TENNESSEE, INC.
Category: prescription | Type: HUMAN PRESCRIPTION DRUG LABEL
Date: 20111027

ACTIVE INGREDIENTS: VARDENAFIL HYDROCHLORIDE 5 mg/1 1
INACTIVE INGREDIENTS: CELLULOSE, MICROCRYSTALLINE; CROSPOVIDONE; SILICON DIOXIDE; MAGNESIUM STEARATE; HYPROMELLOSES; POLYETHYLENE GLYCOL; TITANIUM DIOXIDE; FERRIC OXIDE YELLOW; FERRIC OXIDE RED

Vardenafil HCl (Levitra®) Tablets

DESCRIPTION

LEVITRA® is an oral therapy for the treatment of erectile dysfunction. This monohydrochloride salt of vardenafil is a selective inhibitor of cyclic guanosine monophosphate (cGMP)-specific phosphodiesterase type 5 (PDE5).

Vardenafil HCl is designated chemically as piperazine, 1-[[3-(1,4-dihydro-5-methyl-4-oxo-7-propylimidazo[5,1-f ][1,2,4]triazin-2-yl)-4-ethoxyphenyl]sulfonyl]-4-ethyl-, monohydrochloride and has the following structural formula:

Vardenafil HCl is a nearly colorless, solid substance with a molecular weight of 579.1 g/mol and a solubility of 0.11 mg/mL in water. LEVITRA is formulated as orange, round, film-coated tablets with “BAYER” cross debossed on one side and “2.5”, “5”, “10”, and “20” on the other side corresponding to 2.5 mg, 5 mg, 10 mg, and 20 mg of vardenafil, respectively. In addition to the active ingredient, vardenafil HCl, each tablet contains microcrystalline cellulose, crospovidone, colloidal silicon dioxide, magnesium stearate, hypromellose, polyethylene glycol, titanium dioxide, yellow ferric oxide, and red ferric oxide.

CLINICAL PHARMACOLOGY

Mechanism of Action

Penile erection is a hemodynamic process initiated by the relaxation of smooth muscle in the corpus cavernosum and its associated arterioles. During sexual stimulation, nitric oxide is released from nerve endings and endothelial cells in the corpus cavernosum. Nitric oxide activates the enzyme guanylate cyclase resulting in increased synthesis of cyclic guanosine monophosphate (cGMP) in the smooth muscle cells of the corpus cavernosum. The cGMP in turn triggers smooth muscle relaxation, allowing increased blood flow into the penis, resulting in erection. The tissue concentration of cGMP is regulated by both the rates of synthesis and degradation via phosphodiesterases (PDEs). The most abundant PDE in the human corpus cavernosum is the cGMP-specific phosphodiesterase type 5 (PDE5); therefore, the inhibition of PDE5 enhances erectile function by increasing the amount of cGMP. Because sexual stimulation is required to initiate the local release of nitric oxide, the inhibition of PDE5 has no effect in the absence of sexual stimulation.

In vitro studies have shown that vardenafil is a selective inhibitor of PDE5. The inhibitory effect of vardenafil is more selective on PDE5 than for other known phosphodiesterases (>15-fold relative to PDE6, >130-fold relative to PDE1, >300-fold relative to PDE11, and >1,000-fold relative to PDE2, 3, 4, 7, 8, 9, and 10).

Pharmacokinetics

The pharmacokinetics of vardenafil are approximately dose proportional over the recommended dose range. Vardenafil is eliminated predominantly by hepatic metabolism, mainly by CYP3A4 and to a minor extent, CYP2C isoforms. Concomitant use with potent CYP3A4 inhibitors such as ritonavir, indinavir, ketoconazole, as well as moderate CYP3A inhibitors such as erythromycin results in significant increases of plasma levels of vardenafil (see PRECAUTIONS, WARNINGS and DOSAGE AND ADMINISTRATION). Mean vardenafil plasma concentrations measured after the administration of a single oral dose of 20 mg to healthy male volunteers are depicted in Figure 1.

Figure 1: Plasma Vardenafil Concentration (Mean ± SD) Curve for a Single 20 mg LEVITRA Dose

Absorption:

Vardenafil is rapidly absorbed with absolute bioavailability of approximately 15%. Maximum observed plasma concentrations after a single 20 mg dose in healthy volunteers are usually reached between 30 minutes and 2 hours (median 60 minutes) after oral dosing in the fasted state. Two food-effect studies were conducted which showed that high-fat meals caused a reduction in Cmax by 18%-50%.

Distribution:

The mean steady-state volume of distribution (Vss) for vardenafil is 208 L, indicating extensive tissue distribution. Vardenafil and its major circulating metabolite, M1, are highly bound to plasma proteins (about 95% for parent drug and M1). This protein binding is reversible and independent of total drug concentrations.

Following a single oral dose of 20 mg vardenafil in healthy volunteers, a mean of 0.00018% of the administered dose was obtained in semen 1.5 hours after dosing.

Metabolism:

Vardenafil is metabolized predominantly by the hepatic enzyme CYP3A4, with contribution from the CYP3A5 and CYP2C isoforms. The major circulating metabolite, M1, results from desethylation at the piperazine moiety of vardenafil. M1 is subject to further metabolism. The plasma concentration of M1 is approximately 26% that of the parent compound. This metabolite shows a phosphodiesterase selectivity profile similar to that of vardenafil and an in vitro inhibitory potency for PDE5 28% of that of vardenafil. Therefore, M1 accounts for approximately 7% of total pharmacologic activity.

Excretion:

The total body clearance of vardenafil is 56 L/h, and the terminal half-life of vardenafil and its primary metabolite (M1) is approximately 4-5 hours. After oral administration, vardenafil is excreted as metabolites predominantly in the feces (approximately 91-95% of administered oral dose) and to a lesser extent in the urine (approximately 2-6% of administered oral dose).

Pharmacokinetics in Special Populations

Pediatrics: Vardenafil trials were not conducted in the pediatric population.

Geriatrics: In a healthy volunteer study of elderly males (≥65 years) and younger males (18–45 years), mean Cmax and AUC were 34% and 52% higher, respectively, in the elderly males (see PRECAUTIONS, Geriatric Use and DOSAGE AND ADMINISTRATION). Consequently, a lower starting dose of LEVITRA (5 mg) in patients ≥65 years of age should be considered.

Renal Insufficiency: In volunteers with mild renal impairment (CLcr = 50-80 ml/min), the pharmacokinetics of vardenafil were similar to those observed in a control group with normal renal function. In the moderate (CLcr = 30-50 ml/min) or severe (CLcr<30 ml/min) renal impairment groups, the AUC of vardenafil was 20–30% higher compared to that observed in a control group with normal renal function (CLcr>80 ml/min). Vardenafil pharmacokinetics have not been evaluated in patients requiring renal dialysis (see PRECAUTIONS, Renal Insufficiency, and DOSAGE AND ADMINISTRATION).

Hepatic Insufficiency: In volunteers with mild hepatic impairment (Child-Pugh A), the Cmax and AUC following a 10 mg vardenafil dose were increased by 22% and 17%, respectively, compared to healthy control subjects. In volunteers with moderate hepatic impairment (Child-Pugh B), the Cmax and AUC following a 10 mg vardenafil dose were increased by 130% and 160%, respectively, compared to healthy control subjects. Consequently, a starting dose of 5 mg is recommended for patients with moderate hepatic impairment, and the maximum dose should not exceed 10 mg (see PRECAUTIONS and DOSAGE AND ADMINISTRATION). Vardenafil has not been evaluated in patients with severe (Child-Pugh C) hepatic impairment.

Pharmacodynamics

Effects on Blood Pressure:

In a clinical pharmacology study of patients with erectile dysfunction, single doses of vardenafil 20 mg caused a mean maximum decrease in supine blood pressure of 7 mmHg systolic and 8 mmHg diastolic (compared to placebo), accompanied by a mean maximum increase of heart rate of 4 beats per minute. The maximum decrease in blood pressure occurred between 1 and 4 hours after dosing. Following multiple dosing for 31 days, similar blood pressure responses were observed on Day 31 as on Day 1. Vardenafil may add to the blood pressure lowering effects of antihypertensive agents (see PRECAUTIONS, Drug Interactions).

Effects on Blood Pressure and Heart Rate when LEVITRA is Combined with Nitrates:

A study was conducted in which the blood pressure and heart rate response to 0.4 mg nitroglycerin (NTG) sublingually was evaluated in 18 healthy subjects following pretreatment with LEVITRA 20 mg at various times before NTG administration. LEVITRA 20 mg caused an additional time-related reduction in blood pressure and increase in heart rate in association with NTG administration. The blood pressure effects were observed when LEVITRA 20 mg was dosed 1 or 4 hours before NTG and the heart rate effects were observed when 20 mg was dosed 1, 4, or 8 hours before NTG. Additional blood pressure and heart rate changes were not detected when LEVITRA 20 mg was dosed 24 hours before NTG. (See Figure 2.)

Figure 2: Placebo-subtracted point estimates (with 90% CI) of mean maximal blood pressure and heart rate effects of pre-dosing with LEVITRA 20 mg at 24, 8, 4, and 1 hour before 0.4 mg NTG sublingually.

Because the disease state of patients requiring nitrate therapy is anticipated to increase the likelihood of hypotension, the use of vardenafil by patients on nitrate therapy or on nitric oxide donors is contraindicated (see CONTRAINDICATIONS).

Electrophysiology:

The effect of 10 mg and 80 mg vardenafil on QT interval was evaluated in a single-dose, double-blind, randomized, placebo- and active-controlled (moxifloxacin 400 mg) crossover study in 59 healthy males (81% White, 12% Black, 7% Hispanic) aged 45-60 years. The QT interval was measured at one hour post dose because this time point approximates the average time of peak vardenafil concentration. The 80 mg dose of LEVITRA (four times the highest recommended dose) was chosen because this dose yields plasma concentrations covering those observed upon co-administration of a low-dose of LEVITRA (5 mg) and 600 mg BID of ritonavir. Of the CYP3A4 inhibitors that have been studied, ritonavir causes the most significant drug-drug interaction with vardenafil. Table 1 summarizes the effect on mean uncorrected QT and mean corrected QT interval (QTc) with different methods of correction (Fridericia and a linear individual correction method) at one hour post-dose. No single correction method is known to be more valid than the other. In this study, the mean increase in heart rate associated with a 10 mg dose of LEVITRA compared to placebo was 5 beats/minute and with an 80 mg dose of LEVITRA the mean increase was 6 beats/minute.

Table 1. Mean QT and QTc changes in msec (90% CI) from baseline relative to placebo at 1 hour post-dose with different methodologies to correct for the effect of heart rate.
Drug/Dose | QT Uncorrected (msec) | Fridericia QT Correction (msec) | Individual QT Correction (msec)
Vardenafil 10 mg | -2 (-4, 0) | 8 (6, 9) | 4 (3, 6)
Vardenafil 80 mg | -2 (-4, 0) | 10 (8, 11) | 6 (4, 7)
Moxifloxacin [Active control (drug known to prolong QT)] 400 mg | 3 (1, 5) | 8 (6, 9) | 7 (5, 8)

Therapeutic and supratherapeutic doses of vardenafil and the active control moxifloxacin produced similar increases in QTc interval. This study, however, was not designed to make direct statistical comparisons between the drug or the dose levels. The clinical impact of these QTc changes is unknown (see PRECAUTIONS).

In a separate postmarketing study of 44 healthy volunteers, single doses of 10 mg LEVITRA resulted in a placebo-subtracted mean change from baseline of QTcF (Fridericia correction) of 5 msec (90% CI: 2,8). Single doses of gatifloxacin 400mg resulted in a placebo-subtracted mean change from baseline QTcF of 4 msec (90% CI: 1,7). When LEVITRA 10mg and gatifloxacin 400 mg were co-administered, the mean QTcF change from baseline was additive when compared to either drug alone and produced a mean QTcF change of 9 msec from baseline (90% CI: 6,11). The clinical impact of these QT changes is unknown (see PRECAUTIONS, Congenital or Acquired QT Prolongation).

Effects on Exercise Treadmill Test in Patients with Coronary Artery Disease (CAD):

In two independent trials that assessed 10 mg (n=41) and 20 mg (n=39) vardenafil, respectively, vardenafil did not alter the total treadmill exercise time compared to placebo. The patient population included men aged 40-80 years with stable exercise-induced angina documented by at least one of the following: 1) prior history of MI, CABG, PTCA, or stenting (not within 6 months); 2) positive coronary angiogram showing at least 60% narrowing of the diameter of at least one major coronary artery; or 3) a positive stress echocardiogram or stress nuclear perfusion study.

Results of these studies showed that LEVITRA did not alter the total treadmill exercise time compared to placebo (10 mg LEVITRA vs. placebo: 433±109 and 426±105 seconds, respectively; 20 mg LEVITRA vs. placebo: 414±114 and 411±124 seconds, respectively). The total time to angina was not altered by LEVITRA when compared to placebo (10 mg LEVITRA vs. placebo: 291±123 and 292±110 seconds; 20 mg LEVITRA vs. placebo: 354±137 and 347±143 seconds, respectively). The total time to 1 mm or greater ST-segment depression was similar to placebo in both the 10 mg and the 20 mg LEVITRA groups (10 mg LEVITRA vs. placebo: 380±108 and 334±108 seconds; 20 mg LEVITRA vs. placebo: 364±101 and 366±105 seconds, respectively).

Effects on Vision:

Single oral doses of phosphodiesterase inhibitors have demonstrated transient dose-related impairment of color discrimination (blue/green) using the Farnsworth-Munsell 100-hue test and reductions in electroretinogram (ERG) b-wave amplitudes, with peak effects near the time of peak plasma levels. These findings are consistent with the inhibition of PDE6 in rods and cones, which is involved in phototransduction in the retina. The findings were most evident one hour after administration, diminishing but still present 6 hours after administration. In a single dose study in 25 normal males, LEVITRA 40 mg, twice the maximum daily recommended dose, did not alter visual acuity, intraocular pressure, fundoscopic and slit lamp findings.

In another double-blind, placebo controlled clinical trial, at least 15 doses of 20 mg vardenafil were administered over 8 weeks versus placebo to 52 males. Thirty-two (32) males (62%) of the patients completed the trial. Retinal function was measured by ERG and FM-100 test 2, 6 and 24 hours after dosing. The trial was designed to detect changes in retinal function that might occur in more than 10% of patients. Vardenafil did not produce clinically significant ERG or FM-100 effects in healthy men compared to placebo. Two patients on vardenafil in the trial reported episodes of transient cyanopsia (objects appear blue).

CLINICAL STUDIES

LEVITRA was evaluated in four major double-blind, randomized, placebo-controlled, fixed-dose, parallel design, multicenter trials in 2431 men aged 20-83 (mean age 57 years; 78% White, 7% Black, 2% Asian, 3% Hispanic and 10% Other/Unknown). The doses of LEVITRA in these studies were 5 mg, 10 mg, and 20 mg. Two of these trials were conducted in the general ED population and two in special ED populations (one in patients with diabetes mellitus and one in post-prostatectomy patients). LEVITRA was dosed without regard to meals on an as needed basis in men with erectile dysfunction (ED), many of whom had multiple other medical conditions. The primary endpoints were assessed at 3 months.

Primary efficacy assessment in all four major trials was by means of the Erectile Function (EF) Domain score of the validated International Index of Erectile Function (IIEF) Questionnaire and two questions from the Sexual Encounter Profile (SEP) dealing with the ability to achieve vaginal penetration (SEP2), and the ability to maintain an erection long enough for successful intercourse (SEP3).

In all four fixed-dose efficacy trials, LEVITRA showed clinically meaningful and statistically significant improvement in the EF Domain, SEP2, and SEP3 scores compared to placebo. The mean baseline EF Domain score in these trials was 11.8 (scores range from 0-30 where lower scores represent more severe disease). LEVITRA (5 mg, 10 mg, and 20 mg) was effective in all age categories (<45, 45 to <65, and ≥65 years) and was also effective regardless of race (White, Black, Other).

Trials in a General Erectile Dysfunction Population: In the major North American fixed-dose trial, 762 patients (mean age 57, range 20-83 years; 79% White, 13% Black, 4% Hispanic, 2% Asian and 2% Other) were evaluated. The mean baseline EF Domain scores were 13, 13, 13, 14 for the LEVITRA 5 mg, 10 mg, 20 mg and placebo groups, respectively. There was significant improvement (p <0.0001) at 3 months with LEVITRA (EF Domain scores of 18, 21, 21, for the 5 mg, 10 mg, and 20 mg dose groups, respectively) compared to the placebo group (EF Domain score of 15). The European trial (total N=803) confirmed these results. The improvement in mean score was maintained at all doses at 6 months in the North American trial.

In the North American trial, LEVITRA significantly improved the rates of achieving an erection sufficient for penetration (SEP2) at doses of 5 mg, 10 mg, and 20 mg compared to placebo (65%, 75%, and 80%, respectively, compared to a 52% response in the placebo group at 3 months; p <0.0001). The European trial confirmed these results.

LEVITRA demonstrated a clinically meaningful and statistically significant increase in the overall per-patient rate of maintenance of erection to successful intercourse (SEP3) (51% on 5 mg, 64% on 10 mg, and 65% on 20 mg, respectively, compared to 32% on placebo; p <0.0001) at 3 months in the North American trial. The European trial showed comparable efficacy. This improvement in mean score was maintained at all doses at 6 months in the North American trial.

Trial in Patients with ED and Diabetes Mellitus: LEVITRA demonstrated clinically meaningful and statistically significant improvement in erectile function in a prospective, fixed-dose (10 and 20 mg LEVITRA), double-blind, placebo-controlled trial of patients with diabetes mellitus (n=439; mean age 57 years, range 33-81; 80% White, 9% Black, 8% Hispanic, and 3% Other).

Significant improvements in the EF Domain were shown in this study (EF Domain scores of 17 on 10 mg LEVITRA and 19 on 20 mg LEVITRA compared to 13 on placebo; p <0.0001).

LEVITRA significantly improved the overall per-patient rate of achieving an erection sufficient for penetration (SEP2) (61% on 10 mg and 64% on 20 mg LEVITRA compared to 36% on placebo; p <0.0001).

LEVITRA demonstrated a clinically meaningful and statistically significant increase in the overall per-patient rate of maintenance of erection to successful intercourse (SEP3) (49% on 10 mg, 54% on 20 mg LEVITRA compared to 23% on placebo; p <0.0001).

Trial in Patients with ED after Radical Prostatectomy: LEVITRA demonstrated clinically meaningful and statistically significant improvement in erectile function in a prospective, fixed-dose (10 and 20 mg LEVITRA), double-blind, placebo-controlled trial in post-prostatectomy patients (n=427, mean age 60, range 44-77 years; 93% White, 5% Black, 2% Other).

Significant improvements in the EF Domain were shown in this study (EF Domain scores of 15 on 10 mg LEVITRA and 15 on 20 mg LEVITRA compared to 9 on placebo; p <0.0001).

LEVITRA significantly improved the overall per-patient rate of achieving an erection sufficient for penetration (SEP2) (47% on 10 mg and 48% on 20 mg LEVITRA compared to 22% on placebo; p <0.0001).

LEVITRA demonstrated a clinically meaningful and statistically significant increase in the overall per-patient rate of maintenance of erection to successful intercourse (SEP3) (37% on 10 mg, 34% on 20 mg LEVITRA compared to 10% on placebo; p <0.0001).

INDICATIONS AND USAGE

LEVITRA is indicated for the treatment of erectile dysfunction.

CONTRAINDICATIONS

Nitrates: Administration of LEVITRA with nitrates (either regularly and/or intermittently) and nitric oxide donors is contraindicated (see CLINICAL PHARMACOLOGY, Pharmacodynamics, Effects on Blood Pressure and Heart Rate when LEVITRA is Combined with Nitrates). Consistent with the effects of PDE5 inhibition on the nitric oxide/cyclic guanosine monophosphate pathway, PDE5 inhibitors may potentiate the hypotensive effects of nitrates. A suitable time interval following LEVITRA dosing for the safe administration of nitrates or nitric oxide donors has not been determined.

Hypersensitivity: LEVITRA is contraindicated for patients with a known hypersensitivity to any component of the tablet.

WARNINGS

Cardiovascular effects

General: Physicians should consider the cardiovascular status of their patients, since there is a degree of cardiac risk associated with sexual activity. In men for whom sexual activity is not recommended because of their underlying cardiovascular status, any treatment for erectile dysfunction, including LEVITRA, generally should not be used.

Left Ventricular Outflow Obstruction: Patients with left ventricular outflow obstruction, e.g., aortic stenosis and idiopathic hypertrophic subaortic stenosis, can be sensitive to the action of vasodilators including Type 5 phosphodiesterase inhibitors.

Blood Pressure Effects: LEVITRA has systemic vasodilatory properties that resulted in transient decreases in supine blood pressure in healthy volunteers (mean maximum decrease of 7 mmHg systolic and 8 mmHg diastolic) (see CLINICAL PHARMACOLOGY, Pharmacodynamics). While this normally would be expected to be of little consequence in most patients, prior to prescribing LEVITRA, physicians should carefully consider whether their patients with underlying cardiovascular disease could be affected adversely by such vasodilatory effects.

Effect of Co-administration of Potent CYP3A4 Inhibitors

Long-term safety information is not available on the concomitant administration of vardenafil with HIV protease inhibitors. Concomitant administration with ritonavir or indinavir substantially increases plasma concentrations of vardenafil. Because ritonavir prolongs LEVITRA elimination half-life (5 to 6-fold), no more than a single 2.5 mg dose of LEVITRA should be taken in a 72-hour period by patients also taking ritonavir. Patients taking indinavir, saquinavir, atazanavir or other potent CYP3A4 inhibitors such as clarithromycin, ketoconazole 400 mg daily, or itraconazole 400 mg daily should not exceed a dose of LEVITRA 2.5 mg once daily. For patients taking ketoconazole 200 mg daily or itraconazole 200 mg daily, a single dose of 5 mg LEVITRA should not be exceeded in a 24-hour period (see PRECAUTIONS,Drug Interactions and DOSAGE AND ADMINISTRATION).

Other Effects

There have been rare reports of prolonged erections greater than 4 hours and priapism (painful erections greater than 6 hours in duration) for this class of compounds, including vardenafil. In the event that an erection persists longer than 4 hours, the patient should seek immediate medical assistance. If priapism is not treated immediately, penile tissue damage and permanent loss of potency may result.

Patient Subgroups Not Studied in Clinical Trials

There are no controlled clinical data on the safety or efficacy of LEVITRA in the following patients; and therefore its use is not recommended until further information is available.

- unstable angina; hypotension (resting systolic blood pressure of <90 mmHg); uncontrolled hypertension (>170/110 mmHg); recent history of stroke, life-threatening arrhythmia, or myocardial infarction (within the last 6 months); severe cardiac failure
- severe hepatic impairment (Child-Pugh C)
- end stage renal disease requiring dialysis
- known hereditary degenerative retinal disorders, including retinitis pigmentosa

PRECAUTIONS

The evaluation of erectile dysfunction should include a determination of potential underlying causes, a medical assessment, and the identification of appropriate treatment.

Before prescribing LEVITRA, it is important to note the following:

Alpha-blockers:

Caution is advised when PDE5 inhibitors are co-administered with alpha-blockers. Phosphodiesterase Type 5 (PDE5) inhibitors, including LEVITRA, and alpha-adrenergic blocking agents are both vasodilators with blood-pressure lowering effects. When vasodilators are used in combination, an additive effect on blood pressure may be anticipated. In some patients, concomitant use of these two drug classes can lower blood pressure significantly (see PRECAUTIONS, Drug Interactions) leading to symptomatic hypotension (e.g., fainting). Consideration should be given to the following:

- Patients should be stable on alpha-blocker therapy prior to initiating a PDE5 inhibitor. Patients who demonstrate hemodynamic instability on alpha-blocker therapy alone are at increased risk of symptomatic hypotension with concomitant use of PDE5 inhibitors.
- In those patients who are stable on alpha-blocker therapy, PDE5 inhibitors should be initiated at the lowest recommended starting dose (see DOSAGE and ADMINISTRATION).
- In those patients already taking an optimized dose of PDE5 inhibitor, alpha-blocker therapy should be initiated at the lowest dose. Stepwise increase in alpha-blocker dose may be associated with further lowering of blood pressure in patients taking a PDE5 inhibitor.
- Safety of combined use of PDE5 inhibitors and alpha-blockers may be affected by other variables, including intravascular volume depletion and other anti-hypertensive drugs.

Hepatic Insufficiency:

In volunteers with moderate impairment (Child-Pugh B), the Cmax and AUC following a 10 mg vardenafil dose were increased 130% and 160%, respectively, compared to healthy control subjects. Consequently, a starting dose of 5 mg is recommended for patients with moderate hepatic impairment and the maximum dose should not exceed 10 mg (see CLINICAL PHARMACOLOGY, Pharmacokinetics in Special Populations, and DOSAGE AND ADMINISTRATION). Vardenafil has not been evaluated in patients with severe hepatic impairment (Child-Pugh C).

Congenital or Acquired QT Prolongation: In a study of the effect of LEVITRA on QT interval in 59 healthy males (see CLINICAL PHARMACOLOGY,Electrophysiology), therapeutic (10 mg) and supratherapeutic (80 mg) doses of LEVITRA and the active control moxifloxacin (400 mg) produced similar increases in QTc interval. A postmarketing study evaluating the effect of combining LEVITRA with another drug of comparable QT effect showed an additive QT effect when compared with either drug alone (see CLINICAL PHARMACOLOGY,Electrophysiology). These observations should be considered in clinical decisions when prescribing LEVITRA to patients with known history of QT prolongation or patients who are taking medications known to prolong the QT interval. Patients taking Class 1A (e.g. quinidine, procainamide) or Class III (e.g. amiodarone, sotalol) antiarrhythmic medications or those with congenital QT prolongation, should avoid using LEVITRA.

Renal Insufficiency:

In patients with moderate (CLcr = 30-50 ml/min) to severe (CLcr<30 ml/min) renal impairment, the AUC of vardenafil was 20 – 30% higher compared to that observed in a control group with normal renal function (CLcr>80 ml/min) (see CLINICAL PHARMACOLOGY, Pharmacokinetics in Special Populations). Vardenafil pharmacokinetics have not been evaluated in patients requiring renal dialysis.

General: In humans, vardenafil alone in doses up to 20 mg does not prolong the bleeding time. There is no clinical evidence of any additive prolongation of the bleeding time when vardenafil is administered with aspirin. Vardenafil has not been administered to patients with bleeding disorders or significant active peptic ulceration. Therefore LEVITRA should be administered to these patients after careful benefit-risk assessment.

Treatment for erectile dysfunction should generally be used with caution by patients with anatomical deformation of the penis (such as angulation, cavernosal fibrosis, or Peyronie’s disease) or by patients who have conditions that may predispose them to priapism (such as sickle cell anemia, multiple myeloma, or leukemia).

The safety and efficacy of LEVITRA used in combination with other treatments for erectile dysfunction have not been studied. Therefore, the use of such combinations is not recommended.

Information for Patients

Physicians should discuss with patients the contraindication of LEVITRA with regular and/or intermittent use of organic nitrates. Patients should be counseled that concomitant use of LEVITRA with nitrates could cause blood pressure to suddenly drop to an unsafe level, resulting in dizziness, syncope, or even heart attack or stroke.

Physicians should inform their patients that in some patients concomitant use of PDE5 inhibitors, including LEVITRA, with alpha-blockers can lower blood pressure significantly leading to symptomatic hypotension (e.g., fainting). Patients prescribed LEVITRA who are taking alpha-blockers should be started on the lowest recommended starting dose of LEVITRA (see Drug Interactions and DOSAGE AND ADMINISTRATION). Patients should be advised of the possible occurrence of symptoms related to postural hypotension and appropriate countermeasures. Patients should be advised to contact the prescribing physician if other anti-hypertensive drugs or new medications that may interact with LEVITRA are prescribed by another healthcare provider.

Physicians should discuss with patients the appropriate use of LEVITRA and its anticipated benefits. It should be explained that sexual stimulation is required for an erection to occur after taking LEVITRA. LEVITRA should be taken approximately 60 minutes before sexual activity. Patients should be counseled regarding the dosing of LEVITRA. Patients should be advised to contact their healthcare provider for dose modification if they are not satisfied with the quality of their sexual performance with LEVITRA or in the case of an unwanted effect. Patients should be advised to contact the prescribing physician if new medications that may interact with LEVITRA are prescribed by another healthcare provider.

Physicians should advise patients to stop use of all PDE5 inhibitors, including LEVITRA, and seek medical attention in the event of sudden loss of vision in one or both eyes. Such an event may be a sign of non-arteritic anterior ischemic optic neuropathy (NAION), a cause of decreased vision, including permanent loss of vision, that has been reported rarely post-marketing in temporal association with the use of all PDE5 inhibitors. It is not possible to determine whether these events were related directly to the use of PDE5 inhibitors or to other factors. Physicians should also discuss with patients the increased risk of NAION in individuals who have already experienced NAION in one eye, including whether such individuals could be adversely affected by use of vasodilators such as PDE5 inhibitors (see POST-MARKETING EXPERIENCE, Ophthalmologic).

Physicians should advise patients to stop taking PDE5 inhibitors, including LEVITRA, and seek prompt medical attention in the event of sudden decrease or loss of hearing. These events, which may be accompanied by tinnitus and dizziness, have been reported in temporal association to the intake of PDE5 inhibitors, including LEVITRA. It is not possible to determine whether these events are related directly to the use of PDE5 inhibitors or to other factors (see ADVERSE REACTIONS).

Physicians should discuss with patients the potential cardiac risk of sexual activity for patients with preexisting cardiovascular risk factors.

The use of LEVITRA offers no protection against sexually transmitted diseases. Counseling of patients about protective measures necessary to guard against sexually transmitted diseases, including the Human Immunodeficiency Virus (HIV), should be considered.

Physicians should inform patients that there have been rare reports of prolonged erections greater than 4 hours and priapism (painful erections greater than 6 hours in duration) for LEVITRA and this class of compounds. In the event that an erection persists longer than 4 hours, the patient should seek immediate medical assistance. If priapism is not treated immediately, penile tissue damage and permanent loss of potency may result.

Drug Interactions

Effect of other drugs on LEVITRA

In vitro studies: Studies in human liver microsomes showed that vardenafil is metabolized primarily by cytochrome P450 (CYP) isoforms 3A4/5, and to a lesser degree by CYP2C9. Therefore, inhibitors of these enzymes are expected to reduce vardenafil clearance (see WARNINGS and DOSAGE AND ADMINISTRATION).

In vivo studies: Cytochrome P450 Inhibitors

Cimetidine (400 mg b.i.d.) had no effect on vardenafil bioavailability (AUC) and maximum concentration (Cmax) of vardenafil when co-administered with 20 mg LEVITRA in healthy volunteers.

Erythromycin (500 mg t.i.d.) produced a 4-fold increase in vardenafil AUC and a 3-fold increase in Cmax when co-administered with LEVITRA 5 mg in healthy volunteers (see DOSAGE AND ADMINISTRATION). It is recommended not to exceed a single 5 mg dose of LEVITRA in a 24-hour period when used in combination with erythromycin.

Ketoconazole (200 mg once daily) produced a 10-fold increase in vardenafil AUC and a 4-fold increase in Cmax when co-administered with LEVITRA (5 mg) in healthy volunteers. A 5-mg LEVITRA dose should not be exceeded when used in combination with 200 mg once daily ketoconazole. Since higher doses of ketoconazole (400 mg daily) may result in higher increases in Cmax and AUC, a single 2.5 mg dose of LEVITRA should not be exceeded in a 24-hour period when used in combination with ketoconazole 400 mg daily (see WARNINGS and DOSAGE AND ADMINISTRATION).

HIV Protease Inhibitors:

Indinavir (800 mg t.i.d.) co-administered with LEVITRA 10 mg resulted in a 16-fold increase in vardenafil AUC, a 7-fold increase in vardenafil Cmax and a 2-fold increase in vardenafil half-life. It is recommended not to exceed a single 2.5 mg LEVITRA dose in a 24-hour period when used in combination with indinavir (see WARNINGS and DOSAGE AND ADMINISTRATION).

Ritonavir (600 mg b.i.d.) co-administered with LEVITRA 5 mg resulted in a 49-fold increase in vardenafil AUC and a 13-fold increase in vardenafil Cmax. The interaction is a consequence of blocking hepatic metabolism of vardenafil by ritonavir, a highly potent CYP3A4 inhibitor, which also inhibits CYP2C9. Ritonavir significantly prolonged the half-life of vardenafil to 26 hours. Consequently, it is recommended not to exceed a single 2.5 mg LEVITRA dose in a 72-hour period when used in combination with ritonavir (see WARNINGS and DOSAGE AND ADMINISTRATION).

Other CYP3A4 inhibitors: Although specific interactions have not been studied, other CYP3A4 inhibitors, including grapefruit juice would likely increase vardenafil exposure.

Other Drug Interactions: No pharmacokinetic interactions were observed between vardenafil and the following drugs: glyburide, warfarin, digoxin, Maalox, and ranitidine. In the warfarin study, vardenafil had no effect on the prothrombin time or other pharmacodynamic parameters.

Effects of LEVITRA on other drugs

In vitro studies:

Vardenafil and its metabolites had no effect on CYP1A2, 2A6, and 2E1 (Ki >100 µM). Weak inhibitory effects toward other isoforms (CYP2C8, 2C9, 2C19, 2D6, 3A4) were found, but Ki values were in excess of plasma concentrations achieved following dosing. The most potent inhibitory activity was observed for vardenafil metabolite M1, which had a Ki of 1.4 µM toward CYP3A4, which is about 20 times higher than the M1 Cmax values after an 80 mg LEVITRA dose.

In vivo studies:

Nitrates: The blood pressure lowering effects of sublingual nitrates (0.4 mg) taken 1 and 4 hours after vardenafil and increases in heart rate when taken at 1, 4 and 8 hours were potentiated by a 20 mg dose of LEVITRA in healthy middle-aged subjects. These effects were not observed when LEVITRA 20 mg was taken 24 hours before the NTG. Potentiation of the hypotensive effects of nitrates for patients with ischemic heart disease has not been evaluated, and concomitant use of LEVITRA and nitrates is contraindicated (see CLINICAL PHARMACOLOGY, Pharmacodynamics, Effects on Blood Pressure and Heart Rate when LEVITRA is Combined with Nitrates;CONTRAINDICATIONS).

Nifedipine: Vardenafil 20 mg, when co-administered with slow-release nifedipine 30 mg or 60 mg once daily, did not affect the relative bioavailability (AUC) or maximum concentration (Cmax) of nifedipine, a drug that is metabolized via CYP3A4. Nifedipine did not alter the plasma levels of LEVITRA when taken in combination. In these patients whose hypertension was controlled with nifedipine, LEVITRA 20 mg produced mean additional supine systolic/diastolic blood pressure reductions of 6/5 mmHg compared to placebo.

Alpha-blockers:

Blood pressure effects in patients on stable alpha-blocker treatment:

Two clinical pharmacology studies were conducted in patients with benign prostatic hyperplasia (BPH) on stable-dose alpha-blocker treatment for at least four weeks.

Study 1: This study was designed to evaluate the effect of 5 mg vardenafil compared to placebo when administered to BPH patients on chronic alpha-blocker therapy in two separate cohorts: tamsulosin 0.4 mg daily (cohort 1, n=21) and terazosin 5 or 10 mg daily (cohort 2, n=21). The design was a randomized, double blind, cross-over study with four treatments: vardenafil 5 mg or placebo administered simultaneously with the alpha-blocker and vardenafil 5 mg or placebo administered 6 hours after the alpha-blocker. Blood pressure and pulse were evaluated over the 6-hour interval after vardenafil dosing. For BP results see Table 2. One patient after simultaneous treatment with 5 mg vardenafil and 10 mg terazosin exhibited symptomatic hypotension with standing blood pressure of 80/60 mmHg occurring one hour after administration and subsequent mild dizziness and moderate lightheadedness lasting for 6 hours. For vardenafil and placebo, five and two patients, respectively, experienced a decrease in standing systolic blood pressure (SBP) of >30 mmHg following simultaneous administration of terazosin. Hypotension was not observed when vardenafil 5 mg and terazosin were administered 6 hours apart. Following simultaneous administration of vardenafil 5 mg and tamsulosin, two patients had a standing SBP of <85 mmHg; two and one patient (vardenafil and placebo, respectively) had a decrease in standing SBP of >30 mmHg. When tamsulosin and vardenafil 5 mg were separated by 6 hours, two patients had a standing SBP <85 mmHg and one patient had a decrease in SBP of >30 mmHg. There were no severe adverse events related to hypotension reported during the study. There were no cases of syncope.

Table 2: Mean (95% C.I.) maximal change from baseline in systolic blood pressure (mmHg) following vardenafil 5 mg in BPH patients on stable alpha-blocker therapy (Study 1)
Alpha-Blocker |  | Simultaneous dosing of Vardenafil 5 mg and Alpha-Blocker, Placebo-Subtracted | Dosing of Vardenafil 5 mg and Alpha-Blocker Separated by 6 Hours, Placebo-Subtracted
Terazosin 5 or 10 mg daily | Standing SBP | -3 (-6.7, 0.1) | -4 (-7.4, -0.5)
Terazosin 5 or 10 mg daily | Supine SBP | -4 (-6.7, -0.5) | -4 (-7.1, -0.7)
Tamsulosin 0.4 mg daily | Standing SBP Supine SBP | -6 (-9.9, -2.1) -4 (-7.0, -0.8) | -4 (-8.3, -0.5) -5 (-7.9, -1.7)

Blood pressure effects (standing SBP) in normotensive men on stable dose tamsulosin 0.4 mg following simultaneous administration of vardenafil 5 mg or placebo, or following administration of vardenafil 5 mg or placebo separated by 6 hours are shown in Figure 3. Blood pressure effects (standing SBP) in normotensive men on stable dose terazosin (5 or 10 mg) following simultaneous administration of vardenafil 5 mg or placebo, or following administration of vardenafil 5 mg or placebo separated by 6 hours, are shown in Figure 4.

Figure 3: Mean change from baseline in standing systolic blood pressure (mmHg) over 6 hour interval following simultaneous or 6 hr separation administration of vardenafil 5 mg or placebo with stable dose tamsulosin 0.4 mg in normotensive BPH patients (Study 1)
Figure 4: Mean change from baseline in standing systolic blood pressure (mmHg) over 6 hour interval following simultaneous or 6 hr separation administration of vardenafil 5 mg or placebo with stable dose terazosin (5 or 10 mg) in normotensive BPH patients (Study 1)

Study 2: This study was designed to evaluate the effect of 10 mg vardenafil (stage 1) and 20 mg vardenafil (stage 2) compared to placebo, when administered to a single cohort of BPH patients (n=23) on stable therapy with tamsulosin 0.4 mg or 0.8 mg daily for at least four weeks. The design was a randomized, double blind, two-period cross-over study. Vardenafil or placebo was given simultaneously with tamsulosin. Blood pressure and pulse were evaluated over the 6-hour interval after vardenafil dosing. For BP results see Table 3. One patient experienced a decrease from baseline in standing SBP of >30 mmHg following vardenafil 10 mg. There were no other instances of outlier blood pressure values (standing SBP <85 mmHg or decrease from baseline in standing SBP of >30 mmHg). Three patients reported dizziness following vardenafil 20 mg. There were no cases of syncope.

Table 3: Mean (95% C.I.) maximal change from baseline in systolic blood pressure (mmHg) following vardenafil 10 and 20 mg in BPH patients on stable alpha-blocker therapy with tamsulosin 0.4 or 0.8 mg daily (Study 2)
 | Vardenafil 10 mg Placebo-subtracted | Vardenafil 20 mg Placebo-subtracted
Standing SBP | -4 (-6.8, -0.3) | -4 (-6.8, -1.4)
Supine SBP | -5 (-8.2, -0.8) | -4 (-6.3, -1.8)

Blood pressure effects (standing SBP) in normotensive men on stable dose tamsulosin 0.4 mg following simultaneous administration of vardenafil 20 mg or placebo, or following administration of vardenafil 20 mg or placebo separated by 6 hours are shown in Figure 5.

Figure 5: Mean change from baseline in standing systolic blood pressure (mmHg) over 6 hour interval following simultaneous administration of vardenafil 10 mg (Stage 1), vardenafil 20 mg (Stage 2), or placebo with stable dose tamsulosin 0.4 mg in normotensive BPH patients (Study 2)

Concomitant treatment with vardenafil and alpha-blockers should be initiated only if the patient is stable on his alpha-blocker therapy. In those patients who are stable on alpha-blocker therapy, LEVITRA should be initiated at the lowest recommended starting dose (see DOSAGE and ADMINISTRATION).

Blood pressure effects in normotensive men after forced titration with alpha-blockers:

Two randomized, double blind, placebo-controlled clinical pharmacology studies with healthy normotensive volunteers (age range, 45-74 years) were performed after forced titration of the alpha-blocker terazosin to 10 mg daily over 14 days (n=29), and after initiation of tamsulosin 0.4 mg daily for five days (n=24). There were no severe adverse events related to hypotension in either study. Symptoms of hypotension were a cause for withdrawal in 2 subjects receiving terazosin and in 4 subjects receiving tamsulosin. Instances of outlier blood pressure values (defined as standing SBP <85 mmHg and/or a decrease from baseline of standing SBP >30 mmHg) were observed in 9/24 subjects receiving tamsulosin and 19/29 receiving terazosin. The incidence of subjects with standing SBP <85 mmHg given vardenafil and terazosin to achieve simultaneous Tmax led to early termination of that arm of the study. In most (7/8) of these subjects, instances of standing SBP <85 mmHg were not associated with symptoms. Among subjects treated with terazosin, outlier values were observed more frequently when vardenafil and terazosin were given to achieve simultaneous Tmax than when dosing was administered to separate Tmax by 6 hours. There were 3 cases of dizziness observed with concomitant administration of terazosin and vardenafil. Seven subjects experienced dizziness mainly occurring with simultaneous Tmax administration of tamsulosin. There were no cases of syncope.

Table 4. Mean (95% C.I.) maximal change in baseline in systolic blood pressure (mmHg) following vardenafil 10 and 20 mg in healthy volunteers on daily alpha-blocker therapy
 |  | Dosing of Vardenafil and Alpha-Blocker Separated by 6 Hours |  | Simultaneous dosing of Vardenafil and Alpha-Blocker
Alpha-Blocker |  | Vardenafil 10 mg Placebo-Subtracted | Vardenafil 20 mg Placebo-Subtracted | Vardenafil 10 mg Placebo-Subtracted | Vardenafil 20 mg Placebo-Subtracted
Terazosin 10 mg daily | Standing SBP | -7 (-10, -3) | -11 (-14, -7) | -23 (-31, 16) [Due to the sample size, confidence intervals may not be an accurate measure for these data. These values represent the range for the difference.] | -14 (-33, 11)
Terazosin 10 mg daily | Supine SBP | -5 (-8, -2) | -7 (-11, -4) | -7 (-25, 19) | -7 (-31, 22)
Tamsulosin 0.4 mg daily | Standing SBP | -4 (-8, -1) | -8 (-11, -4) | -8 (-14, -2) | -8 (-14, -1)
 | Supine SBP | -4 (-8, 0) | -7 (-11, -3) | -5 (-9, -2) | -3 (-7, 0)

Figure 6: Mean change from baseline in standing systolic blood pressure (mmHg) over 6 hour interval following simultaneous or 6 hr separation administration of vardenafil 10 mg, vardenafil 20 mg or placebo with terazosin (10 mg) in healthy volunteers
Figure 7: Mean change from baseline in standing systolic blood pressure (mmHg) over 6 hour interval following simultaneous or 6 hr separation administration of vardenafil 10 mg, vardenafil 20 mg or placebo with tamsulosin (0.4 mg) in healthy volunteers

Ritonavir and indinavir: Upon concomitant administration of 5 mg of LEVITRA with 600 mg BID ritonavir, the Cmax and AUC of ritonavir were reduced by approximately 20%. Upon administration of 10 mg of LEVITRA with 800 mg TID indinavir, the Cmax and AUC of indinavir were reduced by 40% and 30%, respectively.

Alcohol: Alcohol (0.5 g/kg body weight: approximately 40 mL of absolute alcohol in a 70 kg person) and vardenafil plasma levels were not altered when dosed simultaneously. LEVITRA (20 mg) did not potentiate the hypotensive effects of alcohol during the 4-hour observation period in healthy volunteers when administered with alcohol (0.5 g/kg body weight).

Aspirin: LEVITRA (10 mg and 20 mg) did not potentiate the increase in bleeding time caused by aspirin (two 81 mg tablets).

Other interactions: LEVITRA had no effect on the pharmacodynamics of glyburide (glucose and insulin concentrations) and warfarin (prothrombin time or other pharmacodynamic parameters).

Carcinogenesis, Mutagenesis, Impairment of Fertility

Vardenafil was not carcinogenic in rats and mice when administered daily for 24 months. In these studies systemic drug exposures (AUCs) for unbound (free) vardenafil and its major metabolite were approximately 400- and 170-fold for male and female rats, respectively, and 21- and 37-fold for male and female mice, respectively, the exposures observed in human males given the Maximum Recommended Human Dose (MRHD) of 20 mg. Vardenafil was not mutagenic as assessed in either the in vitro bacterial Ames assay or the forward mutation assay in Chinese hamster V79 cells. Vardenafil was not clastogenic as assessed in either the in vitro chromosomal aberration test or the in vivo mouse micronucleus test. Vardenafil did not impair fertility in male and female rats administered doses up to 100 mg/kg/day for 28 days prior to mating in male, and for 14 days prior to mating and through day 7 of gestation in females. In a corresponding 1-month rat toxicity study, this dose produced an AUC value for unbound vardenafil 200 fold greater than AUC in humans at the MRHD of 20 mg.

There was no effect on sperm motility or morphology after single 20 mg oral doses of vardenafil in healthy volunteers.

Pregnancy, Nursing Mothers and Pediatric Use

LEVITRA is not indicated for use in women, newborns, or children. Vardenafil was secreted into the milk of lactating rats at concentrations approximately 10-fold greater than found in the plasma. Following a single oral dose of 3 mg/kg, 3.3% of the administered dose was excreted into the milk within 24 hours. It is not known if vardenafil is excreted in human breast milk.

Pregnancy Category B:

No evidence of specific potential for teratogenicity, embryotoxicity or fetotoxicity was observed in rats and rabbits that received vardenafil at up to 18 mg/kg/day during organogenesis. This dose is approximately 100 fold (rat) and 29 fold (rabbit) greater than the AUC values for unbound vardenafil and its major metabolite in humans given the MRHD of 20 mg. In the rat pre-and postnatal development study, the NOAEL (no observed adverse effect level) for maternal toxicity was 8 mg/kg/day. Retarded physical development of pups in the absence of maternal effects was observed following maternal exposure to 1 and 8 mg/kg possibly due to vasodilatation and/or secretion of the drug into milk. The number of living pups born to rats exposed pre- and postnatally was reduced at 60 mg/kg/day. Based on the results of the pre- and postnatal study, the developmental NOAEL is less than 1 mg/kg/day. Based on plasma exposures in the rat developmental toxicity study, 1 mg/kg/day in the pregnant rat is estimated to produce total AUC values for unbound vardenafil and its major metabolite comparable to the human AUC at the MRHD of 20 mg. There are no adequate and well-controlled trials of vardenafil in pregnant women.

Geriatric Use

Elderly males age 65 years and older have higher vardenafil plasma concentrations than younger males (18 – 45 years), mean Cmax and AUC were 34% and 52% higher, respectively (see CLINICAL PHARMACOLOGY, Pharmacokinetics in Special Populations, and DOSAGE AND ADMINISTRATION). Phase 3 clinical trials included more than 834 elderly patients, and no differences in safety or effectiveness of LEVITRA 5, 10, or 20 mg were noted when these elderly patients were compared to younger patients. However, due to increased vardenafil concentrations in the elderly, a starting dose of 5 mg LEVITRA should be considered in patients ≥65 years of age.

ADVERSE REACTIONS

LEVITRA was administered to over 4430 men (mean age 56, range 18-89 years; 81% White, 6% Black, 2% Asian, 2% Hispanic and 9% Other) during controlled and uncontrolled clinical trials worldwide. Over 2200 patients were treated for 6 months or longer, and 880 patients were treated for at least 1 year.

In placebo-controlled clinical trials, the discontinuation rate due to adverse events was 3.4% for LEVITRA compared to 1.1% for placebo.

When LEVITRA was taken as recommended in placebo-controlled clinical trials, the following adverse events were reported (see Table 5).

Table 5: Adverse Events Reported By ≥2% of Patients Treated with LEVITRA and More Frequent on Drug than Placebo in Fixed and Flexible [Flexible dose studies started all patients at LEVITRA 10 mg and allowed decrease in dose to 5 mg or increase in dose to 20 mg based on side effects and efficacy.] Dose Randomized, Controlled Trials of 5 mg, 10 mg, or 20 mg Vardenafil
Adverse Event | Percentage of Patients Reporting Event
 | Placebo N = 1199 | LEVITRA N = 2203
Headache | 4% | 15%
Flushing | 1% | 11%
Rhinitis | 3% | 9%
Dyspepsia | 1% | 4%
Accidental Injury [All the events listed in the above table were deemed to be adverse drug reactions with the exception of accidental injury.] | 2% | 3%
Sinusitis | 1% | 3%
Flu Syndrome | 2% | 3%
Dizziness | 1% | 2%
Increased Creatine Kinase | 1% | 2%
Nausea | 1% | 2%

Back pain was reported in 2.0% of patients treated with LEVITRA and 1.7% of patients on placebo.

Placebo-controlled trials suggested a dose effect in the incidence of some adverse events (headache, flushing, dyspepsia, nausea, rhinitis) over the 5 mg, 10 mg, and 20 mg doses of LEVITRA. The following section identifies additional, less frequent events (<2%) reported during the clinical development of LEVITRA. Excluded from this list are those events that are infrequent and minor, those events that may be commonly observed in the absence of drug therapy, and those events that are not reasonably associated with the drug.

BODY AS A WHOLE: anaphylactic reaction (including laryngeal edema),
asthenia, face edema, pain

AUDITORY: sudden decrease or loss of hearing, tinnitus

CARDIOVASCULAR: angina pectoris, chest pain, hypertension,
hypotension, myocardial ischemia, myocardial infarction, palpitation,
postural hypotension, syncope, tachycardia

DIGESTIVE: abdominal pain, abnormal liver function tests, diarrhea, dry
mouth, dysphagia, esophagitis, gastritis, gastroesophageal reflux, GGTP
increased, vomiting

MUSCULOSKELETAL: arthralgia, back pain, myalgia, neck pain

NERVOUS: hypertonia, hypesthesia, insomnia, paresthesia, somnolence,
vertigo

RESPIRATORY: dyspnea, epistaxis, pharyngitis

SKIN AND APPENDAGES: photosensitivity reaction, pruritus, rash,
sweating

OPHTHALMOLOGIC: abnormal vision, blurred vision, chromatopsia,
changes in color vision, conjunctivitis (increased redness of the eye), dim
vision, eye pain, glaucoma, photophobia, watery eyes

UROGENITAL: abnormal ejaculation, priapism (including prolonged or
painful erections)

POST-MARKETING EXPERIENCE

Ophthalmologic

Non-arteritic anterior ischemic optic neuropathy (NAION), a cause of decreased vision including permanent loss of vision, has been reported rarely post-marketing in temporal association with the use of phosphodiesterase type 5 (PDE5) inhibitors, including LEVITRA. Most, but not all, of these patients had underlying anatomic or vascular risk factors for development of NAION, including but not necessarily limited to: low cup to disc ratio (“crowded disc”), age over 50, diabetes, hypertension, coronary artery disease, hyperlipidemia and smoking. It is not possible to determine whether these events are related directly to the use of PDE5 inhibitors, to the patient’s underlying vascular risk factors or anatomical defects, to a combination of these factors, or to other factors (see PRECAUTIONS, Information for Patients).

Visual disturbances including vision loss (temporary or permanent), such as visual field defect, retinal vein occlusion, and reduced visual acuity, have also been reported rarely in post-marketing experience. It is not possible to determine whether these events are related directly to the use of LEVITRA.

Neurologic

Seizure, seizure recurrence and transient global amnesia have been reported post-marketing in temporal association with LEVITRA.

Otologic

Cases of sudden decrease or loss of hearing have been reported post-marketing in temporal association with the use of PDE5 inhibitors, including LEVITRA. In some cases, medical conditions and other factors were reported that may have also played a role in the otologic adverse events. In many cases, medical follow-up information was limited. It is not possible to determine whether these reported events are related directly to the use of LEVITRA, to the patient’s underlying risk factors for hearing loss, a combination of these factors, or to other factors (see PRECAUTIONS, Information for Patients).

OVERDOSAGE

The maximum dose of LEVITRA for which human data are available is a single 120 mg dose administered to eight healthy male volunteers. The majority of these subjects experienced reversible back pain/myalgia and/or “abnormal vision.”

In cases of overdose, standard supportive measures should be taken as required. Renal dialysis is not expected to accelerate clearance because vardenafil is highly bound to plasma proteins and is not significantly eliminated in the urine.

DOSAGE AND ADMINISTRATION

For most patients, the recommended starting dose of LEVITRA is 10 mg, taken orally approximately 60 minutes before sexual activity. The dose may be increased to a maximum recommended dose of 20 mg or decreased to 5 mg based on efficacy and side effects. The maximum recommended dosing frequency is once per day. LEVITRA can be taken with or without food. Sexual stimulation is required for a response to treatment.

Geriatrics: A starting dose of 5 mg LEVITRA should be considered in patients ≥65 years of age (see CLINICAL PHARMACOLOGY, Pharmacokinetics in Special Populations and PRECAUTIONS).

Hepatic Impairment: For patients with mild hepatic impairment (Child-Pugh A), no dose adjustment of LEVITRA is required. Vardenafil clearance is reduced in patients with moderate hepatic impairment (Child-Pugh B), and a starting dose of 5 mg LEVITRA is recommended. The maximum dose in patients with moderate hepatic impairment should not exceed 10 mg. LEVITRA has not been evaluated in patients with severe hepatic impairment (Child-Pugh C) (see CLINICAL PHARMACOLOGY, Metabolism and Excretion WARNINGS and PRECAUTIONS).

Renal Impairment: For patients with mild (CLcr = 50-80 ml/min), moderate (CLcr = 30-50 ml/min), or severe (CLcr<30 ml/min) renal impairment, no dose adjustment is required. LEVITRA has not been evaluated in patients on renal dialysis (see CLINICAL PHARMACOLOGY, Metabolism and Excretion and PRECAUTIONS).

Concomitant Medications: The dosage of LEVITRA may require adjustment in patients receiving potent CYP3A4 inhibitors such as ketoconazole, itraconazole, ritonavir, indinavir, saquinavir, atazanavir, and clarithromycin as well as in other patients receiving moderate CYP3A4 inhibitors such as erythromycin (see WARNINGS, PRECAUTIONS, Drug Interactions). For ritonavir, a single dose of 2.5 mg LEVITRA should not be exceeded in a 72-hour period. For indinavir, saquinavir, atazanavir, ketoconazole 400 mg daily, itraconazole 400 mg daily, and clarithromycin, a single dose of 2.5 mg LEVITRA should not be exceeded in a 24-hour period. For ketoconazole 200 mg daily, itraconazole 200 mg daily, and erythromycin, a single dose of 5 mg LEVITRA should not be exceeded in a 24-hour period. For alpha-blockers, caution is advised when PDE5 inhibitors, including LEVITRA, are used concomitantly with alpha-blockers because of the potential for an additive effect on blood pressure. In some patients, concomitant use of these two drug classes can lower blood pressure significantly (see PRECAUTIONS,Alpha-blockers and Drug Interactions) leading to symptomatic hypotension (e.g., fainting). Concomitant treatment should be initiated only if the patient is stable on his alpha blocker therapy. In those patients who are stable on alpha-blocker therapy, LEVITRA should be initiated at a dose of 5 mg (2.5 mg when used concomitantly with certain CYP3A4 inhibitors - see Drug Interactions).

HOW SUPPLIED

LEVITRA (vardenafil HCl) is formulated as orange, film-coated round tablets with debossed “BAYER” cross on one side and “5”, “10”, and “20” on the other side equivalent to 5 mg, 10 mg, and 20 mg of vardenafil, respectively.

Count | 5mg | 10mg | 20mg
2 | 43353-744-02 | 43353-741-02 | 43353-748-02
4 |  | 43353-741-04 | 43353-748-04
6 | 43353-744-06 | 43353-741-06 | 43353-748-06
12 |  |  | 43353-748-12
18 |  | 43353-741-18 | 43353-748-18
2160 |  |  | 43353-748-79

Recommended Storage:

Store at 25°C (77°F); excursions permitted to 15-30°C (59-86°F) [see USP Controlled Room Temperature].

Manufactured for:

Bayer HealthCare Pharmaceuticals Inc.
Wayne, NJ 07470

Manufactured in Germany

Distributed By:

GlaxoSmithKline
Research Triangle Park
NC 27709

LEVITRA is a registered trademark of Bayer AG and is used under license by GlaxoSmithKline.

Rx Only

04/11

©2011 Bayer HealthCare Pharmaceuticals Inc.
Printed in U.S.A.

Repackaged by:
APHENA PHARMA SOLUTIONS - TN
Cookeville, TN 38506
20111027AW

Patient Information

LEVITRA® (Luh-VEE-Trah)
(vardenafil HCl) Tablets

Read the Patient Information about LEVITRA before you start taking it and again each time you get a refill. There may be new information. You may also find it helpful to share this information with your partner. This leaflet does not take the place of talking with your doctor. You and your doctor should talk about LEVITRA when you start taking it and at regular checkups. If you do not understand the information, or have questions, talk with your doctor or pharmacist.

WHAT IMPORTANT INFORMATION SHOULD YOU KNOW ABOUT LEVITRA?

LEVITRA can cause your blood pressure to drop suddenly to an unsafe level if it is taken with certain other medicines. With a sudden drop in blood pressure, you could get dizzy, faint, or have a heart attack or stroke.

Do not take LEVITRA if you:

- take any medicines called “nitrates.”
- use recreational drugs called “poppers” like amyl nitrate and butyl nitrate.

(See "Who Should Not Take Levitra?")

Tell all your healthcare providers that you take LEVITRA. If you need emergency medical care for a heart problem, it will be important for your healthcare provider to know when you last took LEVITRA.

WHAT IS LEVITRA?

LEVITRA is a prescription medicine taken by mouth for the treatment of erectile dysfunction (ED) in men.

ED is a condition where the penis does not harden and expand when a man is sexually excited, or when he cannot keep an erection. A man who has trouble getting or keeping an erection should see his doctor for help if the condition bothers him. LEVITRA may help a man with ED get and keep an erection when he is sexually excited.

LEVITRA does not:

- cure ED
- increase a man’s sexual desire
- protect a man or his partner from sexually transmitted diseases, including HIV. Speak to your doctor about ways to guard against sexually transmitted diseases.
- serve as a male form of birth control

LEVITRA is only for men with ED. LEVITRA is not for women or children. LEVITRA must be used only under a doctor’s care.

HOW DOES LEVITRA WORK?

When a man is sexually stimulated, his body’s normal physical response is to increase blood flow to his penis. This results in an erection. LEVITRA helps increase blood flow to the penis and may help men with ED get and keep an erection satisfactory for sexual activity. Once a man has completed sexual activity, blood flow to his penis decreases, and his erection goes away.

WHO CAN TAKE LEVITRA?

Talk to your doctor to decide if LEVITRA is right for you.

LEVITRA has been shown to be effective in men over the age of 18 years who have erectile dysfunction, including men with diabetes or who have undergone prostatectomy.

WHO SHOULD NOT TAKE LEVITRA?

Do not take LEVITRA if you:

- take any medicines called “nitrates” (See “What important information should you know about LEVITRA?”). Nitrates are commonly used to treat angina. Angina is a symptom of heart disease and can cause pain in your chest, jaw, or down your arm.
  Medicines called nitrates include nitroglycerin that is found in tablets, sprays, ointments, pastes, or patches. Nitrates can also be found in other medicines such as isosorbide dinitrate or isosorbide mononitrate. Some recreational drugs called “poppers” also contain nitrates, such as amyl nitrate and butyl nitrate. Do not use LEVITRA if you are using these drugs. Ask your doctor or pharmacist if you are not sure if any of your medicines are nitrates.
- you have been told by your healthcare provider to not have sexual activity because of health problems. Sexual activity can put an extra strain on your heart, especially if your heart is already weak from a heart attack or heart disease.
- are allergic to LEVITRA or any of its ingredients. The active ingredient in LEVITRA is called vardenafil. See the end of this leaflet for a complete list of ingredients.

WHAT SHOULD YOU DISCUSS WITH YOUR DOCTOR BEFORE TAKING LEVITRA?

Before taking LEVITRA, tell your doctor about all your medical problems, including if you:

- have heart problems such as angina, heart failure, irregular heartbeats, or have had a heart attack. Ask your doctor if it is safe for you to have sexual activity.
- have low blood pressure or have high blood pressure that is not controlled
- have had a stroke
- have had a seizure
- or any family members have a rare heart condition known as prolongation of the QT interval (long QT syndrome)
- have liver problems
- have kidney problems and require dialysis
- have retinitis pigmentosa, a rare genetic (runs in families) eye disease
- have ever had severe vision loss, or if you have an eye condition called non-arteritic anterior ischemic optic neuropathy (NAION)
- have stomach ulcers
- have a bleeding problem
- have a deformed penis shape or Peyronie’s disease
- have had an erection that lasted more than 4 hours
- have blood cell problems such as sickle cell anemia, multiple myeloma, or leukemia

CAN OTHER MEDICATIONS AFFECT LEVITRA?

Tell your doctor about all the medicines you take including prescription and non-prescription medicines, vitamins, and herbal supplements. LEVITRA and other medicines may affect each other. Always check with your doctor before starting or stopping any medicines. Especially tell your doctor if you take any of the following:

- medicines called nitrates (See “What important information should you know about LEVITRA?”)
- medicines called alpha-blockers. These include Hytrin® (terazosin HCl), Flomax® (tamsulosin HCl), Cardura® (doxazosin mesylate), Minipress® (prazosin HCl) or Uroxatral® (alfuzosin HCl). Alpha-blockers are sometimes prescribed for prostate problems or high blood pressure. In some patients the use of PDE5 inhibitor drugs, including LEVITRA, with alpha-blockers can lower blood pressure significantly leading to fainting. You should contact the prescribing physician if alpha-blockers or other drugs that lower blood pressure are prescribed by another healthcare provider.
- medicines that treat abnormal heartbeat. These include quinidine, procainamide, amiodarone and sotalol.
- ritonavir (Norvir®) or indinavir sulfate (Crixivan®) saquinavir (Fortavase® or Invirase®) or atazanavir (Reyataz®)
- ketoconazole or itraconazole (such as Nizoral® or Sporanox®)
- erythromycin or clarithromycin
- other medicines or treatments for ED

HOW SHOULD YOU TAKE LEVITRA?

Take LEVITRA exactly as your doctor prescribes. LEVITRA comes in different doses (2.5 mg, 5 mg, 10 mg, and 20 mg). For most men, the recommended starting dose is 10 mg. Take LEVITRA no more than once a day. Doses should be taken at least 24 hours apart. Some men can only take a low dose of LEVITRA because of medical conditions or medicines they take. Your doctor will prescribe the dose that is right for you.

- If you are older than 65 or have liver problems, your doctor may start you on a lower dose of LEVITRA.
- If you have prostate problems or high blood pressure, for which you take medicines called alpha-blockers, your doctor may start you on a lower dose of LEVITRA.
- If you are taking certain other medicines your doctor may prescribe a lower starting dose and limit you to one dose of LEVITRA in a 72-hour (3 days) period.

Take 1 LEVITRA tablet about 1 hour (60 minutes) before sexual activity. Some form of sexual stimulation is needed for an erection to happen with LEVITRA. LEVITRA may be taken with or without meals.

Do not change your dose of LEVITRA without talking to your doctor. Your doctor may lower your dose or raise your dose, depending on how your body reacts to LEVITRA.

If you take too much LEVITRA, call your doctor or emergency room right away.

WHAT ARE THE POSSIBLE SIDE EFFECTS OF LEVITRA?

The most common side effects with LEVITRA are headache, flushing, stuffy or runny nose, indigestion, upset stomach, or dizziness. These side effects usually go away after a few hours. Call your doctor if you get a side effect that bothers you or one that will not go away.

LEVITRA may uncommonly cause:

- an erection that won’t go away (priapism). If you get an erection that lasts more than 4 hours, get medical help right away. Priapism must be treated as soon as possible or lasting damage can happen to your penis including the inability to have erections.
- color vision changes, such as seeing a blue tinge to objects or having difficulty telling the difference between the colors blue and green.

In rare instances, men taking PDE5 inhibitors (oral erectile dysfunction medicines, including LEVITRA) reported a sudden decrease or loss of vision in one or both eyes. It is not possible to determine whether these events are related directly to these medicines, to other factors such as high blood pressure or diabetes, or to a combination of these. If you experience sudden decrease or loss of vision, stop taking PDE5 inhibitors, including LEVITRA, and call a doctor right away.

Sudden loss or decrease in hearing, sometimes with ringing in the ears and dizziness, has been rarely reported in people taking PDE5 inhibitors, including LEVITRA. It is not possible to determine whether these events are related directly to the PDE5 inhibitors, to other diseases or medications, to other factors, or to a combination of factors. If you experience these symptoms, stop taking LEVITRA and contact a doctor right away.

These are not all the side effects of LEVITRA. For more information, ask your doctor or pharmacist.

HOW SHOULD LEVITRA BE STORED?

- Store LEVITRA at room temperature between 59° and 86° F (15° to 30° C).
- Keep LEVITRA and all medicines out of the reach of children.

GENERAL INFORMATION ABOUT LEVITRA.

Medicines are sometimes prescribed for conditions other than those described in patient information leaflets. Do not use LEVITRA for a condition for which it was not prescribed. Do not give LEVITRA to other people, even if they have the same symptoms that you have. It may harm them.

This leaflet summarizes the most important information about LEVITRA. If you would like more information, talk with your healthcare provider. You can ask your doctor or pharmacist for information about LEVITRA that is written for health professionals.

For more information you can also visit www.LEVITRA.com, or call 1-888-825-5249.

WHAT ARE THE INGREDIENTS OF LEVITRA?

Active Ingredient: vardenafil hydrochloride

Inactive Ingredients: microcrystalline cellulose, crospovidone, colloidal silicon dioxide, magnesium stearate, hypromellose, polyethylene glycol, titanium dioxide, yellow ferric oxide, and red ferric oxide.

Norvir (ritonavir) is a trademark of Abbott Laboratories
Crixivan (indinavir sulfate) is a trademark of Merck & Co., Inc.
Invirase or Fortavase (saquinavir mesylate) is a trademark of Roche Laboratories Inc.
Reyataz (atazanavir sulfate) is a trademark of Bristol-Myers Squibb Company
Nizoral (ketoconazole) is a trademark of Johnson & Johnson
Sporanox (itraconazole) is a trademark of Johnson & Johnson
Hytrin (terazosin HCl) is a trademark of Abbott Laboratories
Flomax (tamsulosin HCl) is a trademark of Yamanouchi Pharmaceutical Co., Ltd.
Cardura (doxazosin mesylate) is a trademark of Pfizer Inc.
Minipress (prazosin HCl) is a trademark of Pfizer Inc.
Uroxatral (alfuzosin HCl) is a trademark of Sanofi-Synthelabo

Manufactured for:

Bayer HealthCare Pharmaceuticals Inc.
Wayne, NJ 07470

Manufactured in Germany

Distributed By:

GlaxoSmithKline
Triangle Park NC 27709

LEVITRA is a registered trademark of Bayer AG and is used under license by GlaxoSmithKline.

Rx Only

04/11

©2011 Bayer HealthCare Pharmaceuticals Inc. Printed in U.S.A.

Repackaged by:
APHENA PHARMA SOLUTIONS - TN
Cookeville, TN 38506
20111027AW

PRINCIPAL DISPLAY PANEL

NDC: 43353-744
Vardenafil HCl (Levitra®) 5mg
Rx Only

PRINCIPAL DISPLAY PANEL

NDC: 43353-741
Vardenafil HCl (Levitra®) 10mg
Rx Only

PRINCIPAL DISPLAY PANEL

NDC: 43353-748
Vardenafil HCl (Levitra®) 20mg
Rx Only